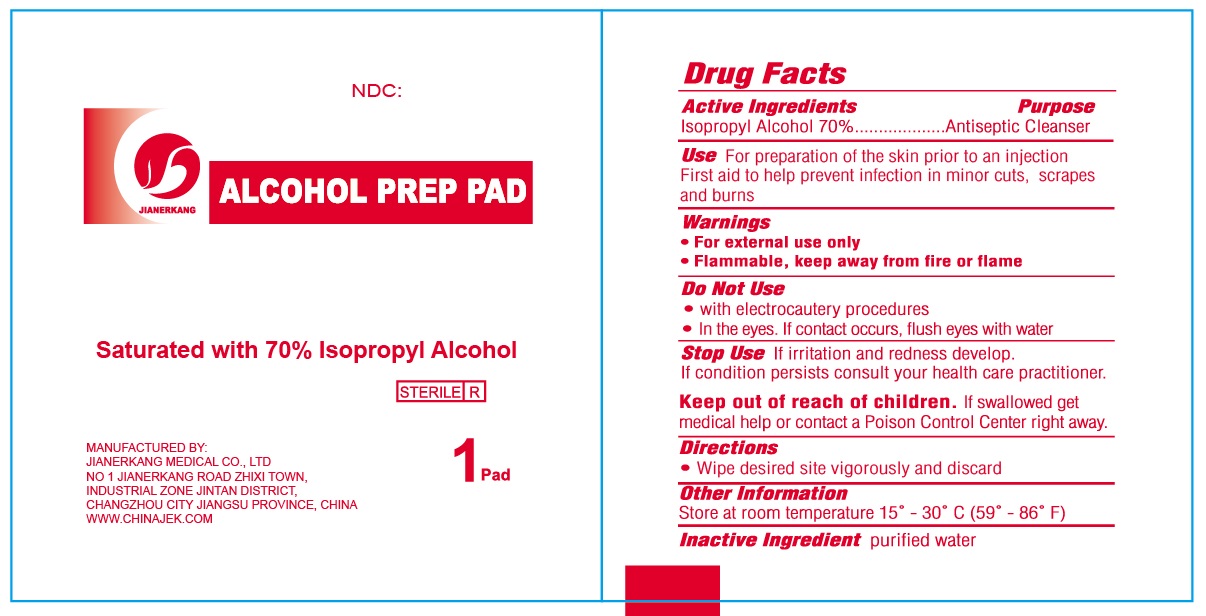 DRUG LABEL: Alcohol Prep Pad
NDC: 34645-5505 | Form: CLOTH
Manufacturer: Jianerkang Medical Co., Ltd
Category: otc | Type: HUMAN OTC DRUG LABEL
Date: 20231023

ACTIVE INGREDIENTS: ISOPROPYL ALCOHOL 70 mL/100 mL
INACTIVE INGREDIENTS: WATER

Alcohol Prep Pad

Active Ingredients

Isopropyl Alcohol 70%

Purpose

Antiseptic Cleanser

Use

For preparation of the skin prior to an injection First aid to help prevent infection in minor cuts, scrapes and burns

Warnings

- For external use only
- Flammable, keep away from fire or flame

Do Not Use

- with electrocautery procedures
- In the eyes, If contact occurs, flush eyes with water

Stop Use

If irritation and redness develop.

If condition persists consult your health care practitioner.

Keep out of reach of children.

If swallowed, get medical help or contact a Poison Control Center right away.

Directions

- Wipe desired site vigorously and discard

Other Information

Store at room temperatue 15° - 30° C (59° - 86° F)

Inactive Ingredient

purified water